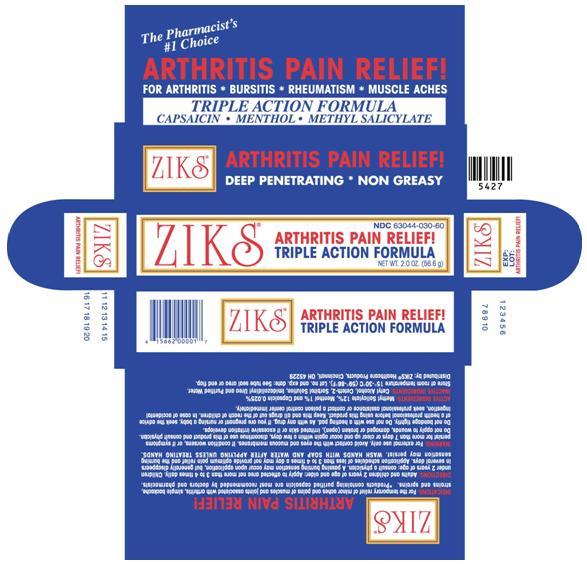 DRUG LABEL: ZIKS ARTHRITIS PAIN RELIEF
NDC: 63044-030 | Form: CREAM
Manufacturer: Nnodum Pharmaceuticals
Category: otc | Type: HUMAN OTC DRUG LABEL
Date: 20251229

ACTIVE INGREDIENTS: METHYL SALICYLATE 6.79 mg/1 g; MENTHOL 0.566 mg/1 g; CAPSAICIN 0.014 mg/1 g
INACTIVE INGREDIENTS: CETYL ALCOHOL; CETETH-20; SORBITOL; UREA; WATER

Arthritis Pain Relief Cream

ACTIVE INGREDIENTS:

Methyl Salicylate 12%, Menthol 1% and Capsaicin 0.025%

ACTIVE INGREDIENTS:

Methyl Salicylate 12%, Menthol 1% and Capsaicin 0.025%

INACTIVE INGREDIENTS:

Cetyl Alcohol, Ceteth-2, Sorbitol Solution, Imidazolidinyl Urea and Purified Water.

INDICATIONS:

For the temporary relief of minor aches and pain of muscles and joints associated with arthritis, simple backache, strains and sprains. *Products containing purified capsaicin are most recommended by doctors and pharmacists.

DIRECTIONS:

Adults and children 2 years of age and older: Apply to affected area not more than 3 to 4 times daily. Children under 2 years of age: consult a physician. A passing burning sensation may occur upon application, but generally disappears in several days. Application schedules of less than 3 to 4 times a day may not provide optimum pain relief ant the burning sensation may persist. WASH HANDS WITH SOAP AND WATER AFTER APPLYING UNLESS TREATING HANDS.

WARNING:

For external use only. Avoid contact with eyes and mucus membranes. If conditions worsens, or if symptoms persist for more than 7 days or clear up and occur again within a few days, discontinue use of this product and consult a physician. Do not apply to wounds, damage or broken (open), irritated skin or excessive irritation develops.

Do not bandage tightly. Do not use with heating pad. As with any drug, if you are pregnant or nursing a baby, seek the advice of a health professional before using this product. Keep this and all drugs out of the reach of children. In case of accidental ingestion, seek professional assistance or contact a poison control center immediately.

Storage

Store at room temperature 15-30 degrees C (59-86 degrees F). Lot number and expiration date: See tube seal area or end flap.

How Supplied:

Ziks cream is supplied in a 2 oz. tube.

Distributed by: ZIKS Healthcare Products, Cincinnati, OH 45229